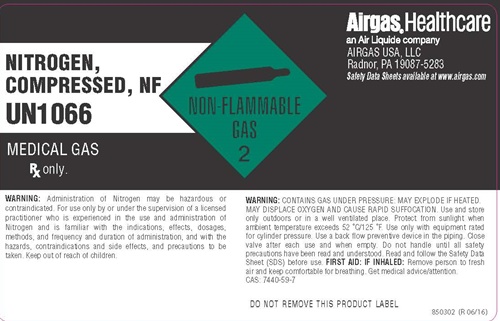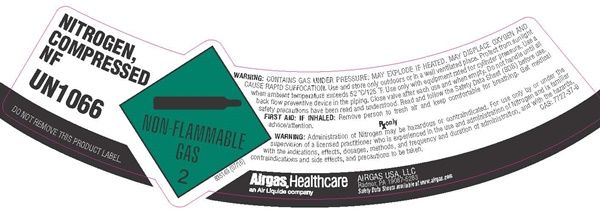 DRUG LABEL: NITROGEN
NDC: 11054-005 | Form: GAS
Manufacturer: AIRGAS USA, LLC
Category: prescription | Type: HUMAN PRESCRIPTION DRUG LABEL
Date: 20251229

ACTIVE INGREDIENTS: Nitrogen 992 mL/1 L

Nitrogen, NF - 005

Nitrogen Compressed, NF product label

NITROGEN, COMPRESSED, NF

UN1066

MEDICAL GAS

Rx only.

NON-FLAMMABLE GAS 2

WARNING: Administration of Nitrogen may be hazardous or contraindicated. For use only by or under the supervision of a licensed practitioner who is experienced in the use and administration of Nitrogen and is familiar with the indications, effects, dosages, methods and frequency and duration of administration, and with the hazards, contraindications and side effects, and precautions to be taken. Keep out of reach of children.

WARNING: CONTAINS GAS UNDER PRESSURE: MAY EXPLODE IF HEATED. MAY DISPLACE OXYGEN AND CAUSE RAPID SUFFOCATION. Use and store only out doors or in a well ventilated place. Protect from sunlight when anbient temperature exceeds 52°C/125°F. Use only with equipment rated for cylinder pressure. Use a back flow preventive device in the piping. Close valve after each use and when empty. Do not handle until all safety precautions have been read and understood. Read and follow the Safety Data Sheet (SDS) before use. FIRST AID: IF INHALED: Remove the person to fresh air and keep comfortable for breathing. Get medical advice/attention.

CAS: 7440-59-7

DO NOT REMOVE THIS PRODUCT LABEL

850302 (R 06/16)

AIRGAS® Healthcare
an Air Liquide Company AIRGAS USA, LLC
Radnor, PA 19087-5283

Safety Data Sheets available at www.airgas.com

NITROGEN, COMPRESSED, NF

UN1066

DO NOT REMOVE THIS PRODUCT LABEL

NON-FLAMMABLE GAS 2

WARNING: CONTAINS GAS UNDER PRESSURE: MAY EXPLODE IF HEATED. MAY DISPLACE OXYGEN AND CAUSE RAPID SUFFOCATION. Use and store only out doors or in a well ventilated place. Protect from sunlight when ambient temperature exceeds 52°C/125°F. Use only with equipment rated for cylinder pressure. Use a back flow preventive device in the piping. Close valve after each use and when empty. Do not handle until all safety precautions have been read and understood. Read and follow the Safety Data Sheet (SDS) before use.

FIRST AID: IF INHALED: Remove the person to fresh air and keep comfortable for breathing. Get medical advice/attention.

Rx only

WARNING: Administration of Nitrogen may be hazardous or contraindicated. For use only by or under the supervision of a licensed practitioner who is experienced in the use and administration of Nitrogen and is familiar with the indications, effects, dosages, methods and frequency and duration of administration, and with the hazards, contraindications and side effects, and precautions to be taken.

CAS: 7727-37-9

835149 (07/16)

AIRGAS® Healthcare
an Air Liquide Company
AIRGAS USA, LLC
Radnor, PA 19087-5283

Safety Data Sheets available at www.airgas.com